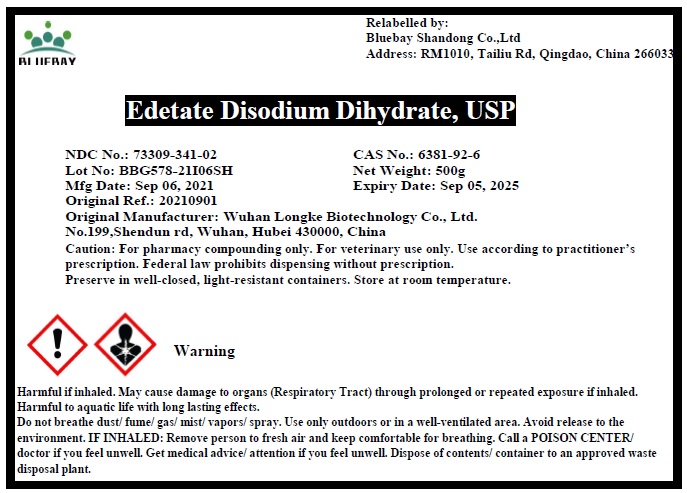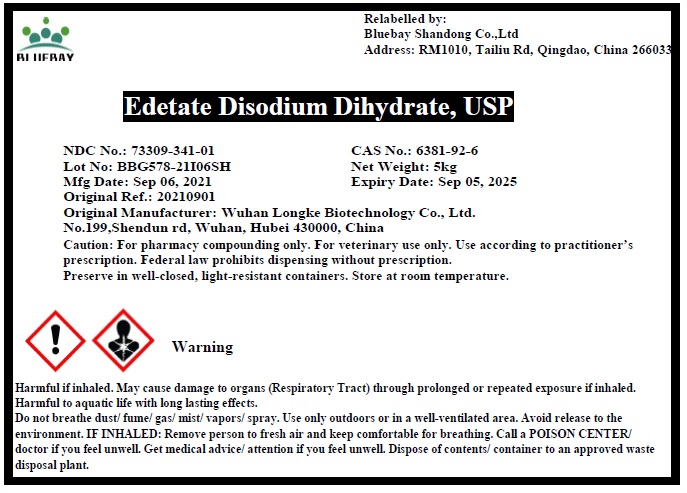 DRUG LABEL: Edetate Disodium Dihydrate
NDC: 73309-341 | Form: POWDER
Manufacturer: BLUEBAY SHANDONG CO.,LTD
Category: other | Type: BULK INGREDIENT
Date: 20211109

ACTIVE INGREDIENTS: EDETATE DISODIUM 1 kg/1 kg

Edetate Disodium Dihydrate